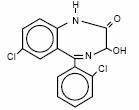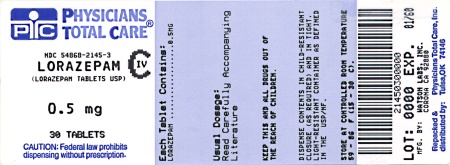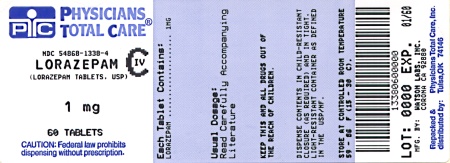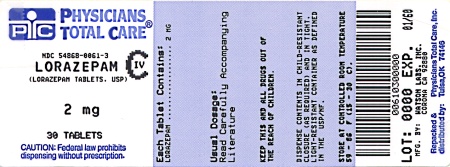 DRUG LABEL: Lorazepam
NDC: 54868-2145 | Form: TABLET
Manufacturer: Physicians Total Care, Inc.
Category: prescription | Type: HUMAN PRESCRIPTION DRUG LABEL
Date: 20100507
DEA Schedule: CIV

ACTIVE INGREDIENTS: LORAZEPAM 0.5 mg/1 1
INACTIVE INGREDIENTS: LACTOSE; MAGNESIUM STEARATE; CELLULOSE, MICROCRYSTALLINE; POLACRILIN POTASSIUM

DESCRIPTION

Lorazepam, an antianxiety agent, has the chemical formula, (±)-7-Chloro-5-(o-chlorophenyl)-1,3-dihydro-3-hydroxy-2H-1,4-benzodiazepin-2-one:

It is a nearly white powder almost insoluble in water. Each lorazepam tablet, to be taken orally, contains 0.5 mg, 1 mg or 2 mg of lorazepam. This product contains the following inactive ingredients: lactose, magnesium stearate, microcrystalline cellulose and polacrilin potassium.

CLINICAL PHARMACOLOGY

Studies in healthy volunteers show that in single high doses lorazepam has a tranquilizing action on the central nervous system with no appreciable effect on the respiratory or cardiovascular systems.

Lorazepam is readily absorbed with an absolute bioavailability of 90 percent. Peak concentrations in plasma occur approximately 2 hours following administration. The peak plasma level of lorazepam from a 2 mg dose is approximately 20 ng/ml.

The mean half-life of unconjugated lorazepam in human plasma is about 12 hours and for its major metabolite, lorazepam glucuronide, about 18 hours. At clinically relevant concentrations, lorazepam is approximately 85% bound to plasma proteins. Lorazepam is rapidly conjugated at its 3-hydroxy group into lorazepam glucuronide which is then excreted in the urine. Lorazepam glucuronide has no demonstrable CNS activity in animals.

The plasma levels of lorazepam are proportional to the dose given. There is no evidence of accumulation of lorazepam on administration up to six months.

Studies comparing young and elderly subjects have shown that the pharmacokinetics of lorazepam remain unaltered with advancing age.

INDICATIONS AND USAGE

Lorazepam is indicated for the management of anxiety disorders or for the short-term relief of the symptoms of anxiety or anxiety associated with depressive symptoms. Anxiety or tension associated with the stress of everyday life usually does not require treatment with an anxiolytic.

The effectiveness of lorazepam in long-term use, that is, more than 4 months, has not been assessed by systematic clinical studies. The physician should periodically reassess the usefulness of the drug for the individual patient.

CONTRAINDICATIONS

Lorazepam is contraindicated in patients with known sensitivity to the benzodiazepines or with acute narrow-angle glaucoma.

WARNINGS

Lorazepam is not recommended for use in patients with a primary depressive disorder of psychosis. As with all patients on CNS-acting drugs, patients receiving lorazepam should be warned not to operate dangerous machinery or motor vehicles and that their tolerance for alcohol and other CNS depressants will be diminished.

PRECAUTIONS

In patients with depression accompanying anxiety, a possibility for suicide should be borne in mind.

For elderly or debilitated patients, the initial daily dosage should not exceed 2 mg in order to avoid oversedation.

Lorazepam dosage should be terminated gradually, since abrupt withdrawal of any antianxiety agent may result in symptoms similar to those for which patients are being treated: anxiety, agitation, irritability, tension, insomnia, and occasional convulsions.

The usual precautions for treating patients with impaired renal or hepatic function should be observed.

In patients where gastrointestinal or cardiovascular disorders coexist with anxiety, it should be noted that lorazepam has not been shown to be of significant benefit in treating the gastrointestinal or cardiovascular component.

Esophageal dilation occurred in rats treated with lorazepam for more than one year at 6 mg/kg/day. The no-effect dose was 1.25 mg/kg/day (approximately 6 times the maximum human therapeutic dose of 10 mg per day). The effect was reversible only when the treatment was withdrawn within two months of first observation of the phenomenon. The clinical significance of this is unknown. However, use of lorazepam for prolonged periods and in geriatric patients requires caution and there should be frequent monitoring for symptoms of upper G.l. disease.

Safety and effectiveness of lorazepam in children of less than 12 years have not been established.

INFORMATION FOR PATIENTS

To assure the safe and effective use of lorazepam, patients should be informed that, since benzodiazepines may produce psychological and physical dependence, it is advisable that they consult with their physician before either increasing the dose or abruptly discontinuing this drug.

ESSENTIAL LABORATORY TESTS

Some patients on lorazepam have developed leukopenia, and some have had elevations of LDH. As with other benzodiazepines, periodic blood counts and liver-function tests are recommended for patients on long-term therapy.

CLINICALLY SIGNIFICANT DRUG INTERACTIONS

The benzodiazepines, including lorazepam, produce CNS-depressant effects when administered with such medications as barbiturates or alcohol.

CARCINOGENESIS AND MUTAGENESIS

No evidence of carcinogenic potential emerged in rats during an 18-month study with lorazepam. No studies regarding mutagenesis have been performed.

PREGNANCY

Reproductive studies in animals were performed in mice, rats, and two strains of rabbits. Occasional anomalies (reduction of tarsals, tibia, metatarsals, malrotated limbs, gastroschisis, malformed skull, and microphthalmia) were seen in drug-treated rabbits without relationship to dosage. Although all of these anomalies were not present in the concurrent control group, they have been reported to occur randomly in historical controls. At doses of 40 mg/kg and higher, there was evidence of fetal resorption and increased fetal loss in rabbits which was not seen at lower doses.

The clinical significance of the above findings is not known. However, an increased risk of congenital malformations associated with the use of minor tranquilizers (chlordiazepoxide, diazepam, and meprobamate) during the first trimester of pregnancy has been suggested in several studies. Because the use of these drugs is rarely a matter of urgency, the use of lorazepam during this period should almost always be avoided. The possibility that a woman of childbearing potential may be pregnant at the time of institution of therapy should be considered. Patients should be advised that if they become pregnant, they should communicate with their physician about the desirability of discontinuing the drug.

In humans, blood levels obtained from umbilical cord blood indicate placental transfer of lorazepam and lorazepam glucuronide.

NURSING MOTHERS

It is not known whether oral lorazepam is excreted in human milk like the other benzodiazepine tranquilizers. As a general rule, nursing should not be undertaken while a patient is on a drug since many drugs are excreted in human milk.

ADVERSE REACTIONS

Adverse reactions, if they occur, are usually observed at the beginning of therapy and generally disappear on continued medication or upon decreasing the dose. In a sample of about 3,500 anxious patients, the most frequent adverse reaction to lorazepam is sedation (15.9%), followed by dizziness (6.9%), weakness (4.2%), and unsteadiness (3.4%). Less frequent adverse reactions are disorientation, depression, nausea, change in appetite, headache, sleep disturbance, agitation, dermatological symptoms, eye-function disturbance, together with various gastrointestinal symptoms and autonomic manifestations. The incidence of sedation and unsteadiness increased with age.

Small decreases in blood pressure have been noted but are not clinically significant, probably being related to the relief of anxiety produced by lorazepam.

Transient amnesia or memory impairment has been reported in association with the use of benzodiazepines.

DRUG ABUSE AND DEPENDENCE

Withdrawal symptoms, similar in character to those noted with barbiturates and alcohol (convulsions, tremor, abdominal and muscle cramps, vomiting, and sweating), have occurred following abrupt discontinuance of lorazepam. The more severe withdrawal symptoms have usually been limited to those patients who received excessive doses over an extended period of time. Generally milder withdrawal symptoms (e.g., dysphoria and insomnia) have been reported following abrupt discontinuance of benzodiazepines taken continuously at therapeutic levels for several months. Consequently, after extended therapy, abrupt discontinuation should generally be avoided and a gradual dosage-tapering schedule followed. Addiction-prone individuals (such as drug addicts or alcoholics) should be under careful surveillance when receiving lorazepam or other psychotropic agents because of the predisposition of such patients to habituation and dependence.

Lorazepam tablets are classified by the Drug Enforcement Administration as a Schedule IV controlled substance.

OVERDOSAGE

In the management of overdosage with any drug, it should be borne in mind that multiple agents may have been taken.

Manifestations of lorazepam overdosage include somnolence, confusion, and coma. Induced vomiting and/or gastric lavage should be undertaken, followed by general supportive care, monitoring of vital signs, and close observation of the patient. Hypotension, though unlikely, usually may be controlled with norepinephrine bitartrate injection. The usefulness of dialysis has not been determined.

Flumazenil, a specific benzodiazepine receptor antagonist, is indicated for the complete or partial reversal of the sedative effects of benzodiazepines and may be used in situations when an overdose with a benzodiazepine is known or suspected. Prior to the administration of flumazenil, necessary measures should be instituted to secure airway, ventilation, and intravenous access. Flumazenil is intended as an adjunct to, not as a substitute for, proper management of benzodiazepine overdose. Patients treated with flumazenil should be monitored for re-sedation, respiratory depression, and other residual benzodiazepine effects for an appropriate period after treatment. The prescriber should be aware of a risk of seizure in association with flumazenil treatment, particularly in long-term benzodiazepine users and in cyclic antidepressant overdose. The complete flumazenil package insert including CONTRAINDICATIONS, WARNINGS, and PRECAUTIONS should be consulted prior to use.

DOSAGE AND ADMINISTRATION

Lorazepam is administered orally. For optimal results, dose, frequency of administration, and duration of therapy should be individualized according to patient response. To facilitate this, 0.5 mg, 1 mg, and 2 mg tablets are available.

The usual range is 2 to 6 mg/day given in divided doses, the largest dose being taken before bedtime, but the daily dosage may vary from 1 to 10 mg/day.

For anxiety, most patients require an initial dose of 2 to 3 mg/day given b.i.d. or t.i.d.

For insomnia due to anxiety or transient situational stress, a single daily dose of 2 to 4 mg may be given, usually at bedtime.

For elderly or debilitated patients, an initial dosage of 1 to 2 mg/day in divided doses is recommended, to be adjusted as needed and tolerated.

The dosage of lorazepam should be increased gradually when needed to help avoid adverse effects. When higher dosage is indicated, the evening dose should be increased before the daytime doses.

HOW SUPPLIED

Lorazepam tablets are available in the following dosage strengths:

0.5 mg: white, scored, round flat faced beveled edge, debossed with 240 over 0.5 on one side and WATSON on the other side, supplied in:

Bottles of 10 | NDC 54868-2145-0
Bottles of 20 | NDC 54868-2145-2
Bottles of 30 | NDC 54868-2145-3
Bottles of 50 | NDC 54868-2145-5
Bottles of 60 | NDC 54868-2145-6
Bottles of 90 | NDC 54868-2145-9
Bottles of 100 | NDC 54868-2145-4

1 mg: white, scored, round flat faced beveled edge, debossed with 241 over 1 on one side and WATSON on the other side, supplied in:

Bottles of 03 | NDC 54868-1338-6
Bottles of 10 | NDC 54868-1338-7
Bottles of 15 | NDC 54868-1338-0
Bottles of 20 | NDC 54868-1338-1
Bottles of 30 | NDC 54868-1338-3
Bottles of 60 | NDC 54868-1338-4
Bottles of 90 | NDC 54868-1338-8
Bottles of 100 | NDC 54868-1338-2
Bottles of 120 | NDC 54868-1338-9

2 mg: white, scored, round flat faced beveled edge, debossed with 242 over 2 on one side and WATSON on the other side, supplied in:

Bottles of 30 | NDC 54868-0061-3
Bottles of 60 | NDC 54868-0061-5
Bottles of 90 | NDC 54868-0061-4
Bottles of 100 | NDC 54868-0061-2
Bottles of 120 | NDC 54868-0061-6

Store at controlled room temperature 15°-30°C (59°-86°F). [See USP.]

Dispense in a tight, light-resistant container as defined in the USP.

Watson Laboratories, Inc.
Corona, CA 92880 USA

30223-3
Rev: February 2004

Repackaging and Relabeling by:
Physicians Total Care, Inc.
Tulsa, OK 74146

PRINCIPAL DISPLAY PANEL

Lorazepam tablets

0.5 mg

1 mg

2 mg